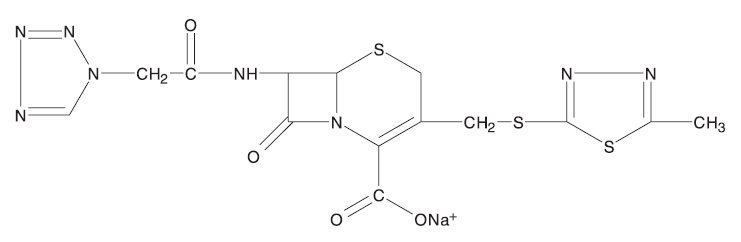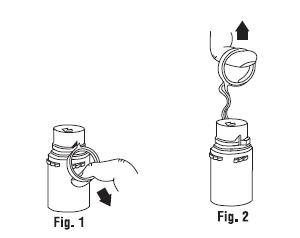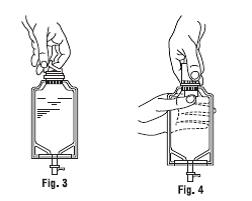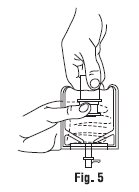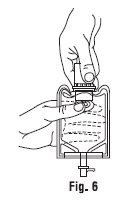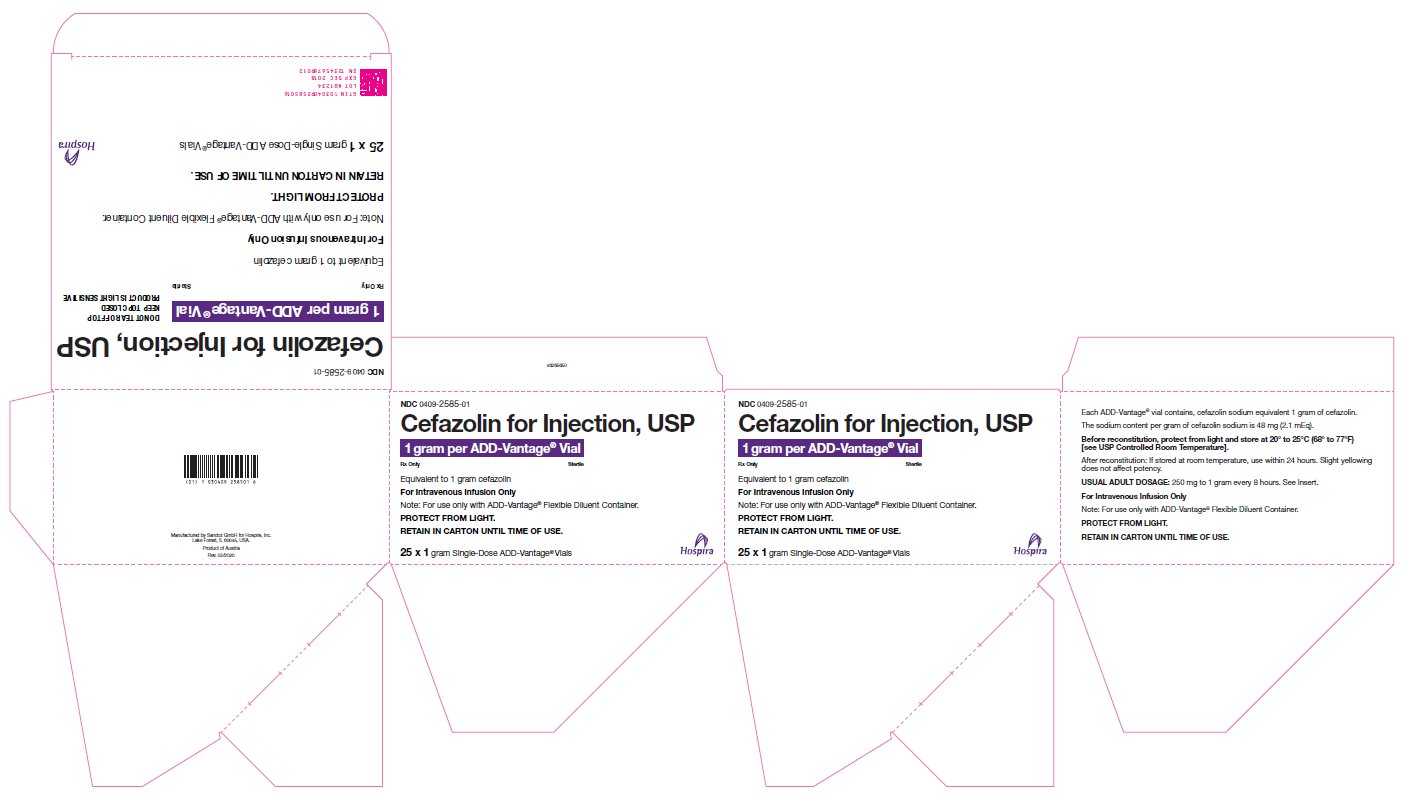 DRUG LABEL: Cefazolin
NDC: 0409-2585 | Form: INJECTION, POWDER, FOR SOLUTION
Manufacturer: Hospira, Inc
Category: prescription | Type: HUMAN PRESCRIPTION DRUG LABEL
Date: 20260121

ACTIVE INGREDIENTS: CEFAZOLIN SODIUM 1 g/1 1

Cefazolin for Injection, USP

ADD-Vantage® Vial

For Intravenous Administration

Rx Only

To reduce the development of drug-resistant bacteria and maintain the effectiveness of cefazolin for injection and other antibacterial drugs, cefazolin for injection should be used only to treat or prevent infections that are proven or strongly suspected to be caused by bacteria.

DESCRIPTION

Cefazolin for injection, USP is a semi-synthetic cephalosporin for parenteral administration. It is the sodium salt of (6R,7R)-3-{[(5-methyl-1,3,4-thiadiazol-2-yl)thio] methyl}-8-oxo-7-[2-(1H-tetrazol-1-yl)acetamido]-5-thia-1-azabicyclo [4.2.0] oct-2-ene-2-carboxylic acid.

Structural Formula:

Molecular Formula: C14H13N8NaO4S3

Molecular Weight: 476.5

The sodium content is 48 mg (2.1 mEq) per 1 gram of cefazolin sodium. Cefazolin for injection, USP is a sterile, white to yellowish powder.

Each ADD-Vantage® vial contains, cefazolin sodium equivalent to 1 gram of cefazolin.

CLINICAL PHARMACOLOGY

Studies have shown that following intravenous administration of cefazolin for injection to normal volunteers, mean serum concentrations peaked at approximately 185 mcg/mL and were approximately 4 mcg/mL at 8 hours for a 1-gram dose.

The serum half-life for cefazolin is approximately 1.8 hours following intravenous administration.

In a study (using normal volunteers) of constant intravenous infusion with dosages of 3.5 mg/kg for one hour (approximately 250 mg) and 1.5 mg/kg the next 2 hours (approximately 100 mg), cefazolin produced a steady serum level at the third hour of approximately 28 mcg/mL.

Studies in patients hospitalized with infections indicate that cefazolin produces mean peak serum levels approximately equivalent to those seen in normal volunteers.

Bile levels in patients without obstructive biliary disease can reach or exceed serum levels by up to five times; however, in patients with obstructive biliary disease, bile levels of cefazolin are considerably lower than serum levels (<1 mcg/mL).

In synovial fluid, the level of cefazolin becomes comparable to that reached in serum at about 4 hours after drug administration.

Studies of cord blood show prompt transfer of cefazolin across the placenta. Cefazolin is present in very low concentrations in the milk of nursing mothers.

Cefazolin is excreted unchanged in the urine. In the first 6 hours approximately 60% of the drug is excreted in the urine and this increases to 70% to 80% within 24 hours.

In patients undergoing peritoneal dialysis (2 L/hour.), cefazolin produced mean serum levels of approximately 10 and 30 mcg/mL after 24 hours’ instillation of a dialyzing solution containing 50 mg/L and 150 mg/L, respectively. Mean peak levels were 29 mcg/mL (range 13 to 44 mcg/mL) with 50 mg/L (3 patients), and 72 mcg/mL (range 26 to 142 mcg/mL) with 150 mg/L (6 patients). Intraperitoneal administration of cefazolin for injection is usually well tolerated.

Controlled studies on adult normal volunteers, receiving 1 gram 4 times a day for 10 days, monitoring CBC, SGOT, SGPT, bilirubin, alkaline phosphatase, BUN, creatinine and urinalysis, indicated no clinically significant changes attributed to cefazolin.

Microbiology

Mechanism of Action

Cefazolin is a bactericidal agent that acts by inhibition of bacterial cell wall synthesis.

Resistance

Predominant mechanisms of bacterial resistance to cephalosporins include the presence of extended-spectrum beta-lactamases and enzymatic hydrolysis.

Antimicrobial Activity

Cefazolin has been shown to be active against most isolates of the following microorganisms, both in vitro and in clinical infections as described in the INDICATIONS AND USAGE (1) section.

Gram-Positive Bacteria

Staphylococcus aureus

Staphylococcus epidermidis

Streptococcus agalactiae

Streptococcus pneumoniae

Streptococcus pyogenes

Methicillin-resistant staphylococci are uniformly resistant to cefazolin.

Gram-Negative Bacteria

Escherichia coli

Proteus mirabilis

Most isolates of indole positive Proteus (Proteus vulgaris), Enterobacter spp., Morganella morganii, Providencia rettgeri, Serratia spp., and Pseudomonas spp. are resistant to cefazolin.

Susceptibility Testing

For specific information regarding susceptibility test interpretive criteria and associated test methods and quality control standards recognized by FDA for this drug, please see: https://www.fda.gov/STIC.

INDICATIONS AND USAGE

Cefazolin for injection is indicated in the treatment of the following serious infections due to susceptible organisms:

Respiratory Tract Infections: Due to S. pneumoniae, Klebsiella species, H. influenzae, S. aureus (penicillin-sensitive and penicillin-resistant), and group A beta-hemolytic streptococci.

Injectable benzathine penicillin is considered to be the drug of choice in treatment and prevention of streptococcal infections, including the prophylaxis of rheumatic fever.

Cefazolin for injection is effective in the eradication of streptococci from the nasopharynx; however, data establishing the efficacy of cefazolin in the subsequent prevention of rheumatic fever are not available at present.

Urinary Tract Infections: Due to E. coli, P. mirabilis, Klebsiella species, and some strains of enterobacter and enterococci.

Skin and Skin Structure Infections: Due to S. aureus (penicillin-sensitive and penicillin-resistant), group A beta-hemolytic streptococci, and other strains of streptococci.

Biliary Tract Infections: Due to E. coli, various strains of streptococci, P. mirabilis, Klebsiella species, and S. aureus.

Bone and Joint Infections: Due to S. aureus.

Genital Infections: (i.e., prostatitis, epididymitis) due to E. coli, P. mirabilis, Klebsiella species, and some strains of enterococci.

Septicemia: Due to S. pneumoniae, S. aureus (penicillin-sensitive and penicillin-resistant), P. mirabilis, E. coli, and Klebsiella species.

Endocarditis: Due to S. aureus (penicillin-sensitive and penicillin-resistant) and group A beta-hemolytic streptococci.

Perioperative Prophylaxis: The prophylactic administration of cefazolin for injection preoperatively, intraoperatively, and postoperatively may reduce the incidence of certain postoperative infections in patients undergoing surgical procedures which are classified as contaminated or potentially contaminated (e.g., vaginal hysterectomy, and cholecystectomy in high-risk patients such as those older than 70 years, with acute cholecystitis, obstructive jaundice, or common duct bile stones).

The perioperative use of cefazolin for injection may also be effective in surgical patients in whom infection at the operative site would present a serious risk (e.g., during open-heart surgery and prosthetic arthroplasty).

The prophylactic administration of cefazolin for injection should usually be discontinued within a 24-hour period after the surgical procedure. In surgery where the occurrence of infection may be particularly devastating (e.g., open-heart surgery and prosthetic arthroplasty), the prophylactic administration of cefazolin for injection may be continued for 3 to 5 days following the completion of surgery.

If there are signs of infection, specimens for cultures should be obtained for the identification of the causative organism so that appropriate therapy may be instituted (see DOSAGE AND ADMINISTRATION).

To reduce the development of drug-resistant bacteria and maintain the effectiveness of cefazolin for injection and other antibacterial drugs, cefazolin for injection should be used only to treat or prevent infections that are proven or strongly suspected to be caused by susceptible bacteria. When culture and susceptibility information are available, they should be considered in selecting or modifying antibacterial therapy. In the absence of such data, local epidemiology and susceptibility patterns may contribute to the empiric selection of therapy.

CONTRAINDICATIONS

CEFAZOLIN FOR INJECTION IS CONTRAINDICATED IN PATIENTS WITH KNOWN ALLERGY TO THE CEPHALOSPORIN GROUP OF ANTIBIOTICS.

WARNINGS

BEFORE THERAPY WITH CEFAZOLIN FOR INJECTION IS INSTITUTED, CAREFUL INQUIRY SHOULD BE MADE TO DETERMINE WHETHER THE PATIENT HAS HAD PREVIOUS HYPERSENSITIVITY REACTIONS TO CEFAZOLIN, CEPHALOSPORINS, PENICILLINS, OR OTHER DRUGS. IF THIS PRODUCT IS GIVEN TO PENICILLIN-SENSITIVE PATIENTS, CAUTION SHOULD BE EXERCISED BECAUSE CROSS-HYPERSENSITIVITY AMONG BETA-LACTAM ANTIBIOTICS HAS BEEN CLEARLY DOCUMENTED AND MAY OCCUR IN UP TO 10% OF PATIENTS WITH A HISTORY OF PENICILLIN ALLERGY. IF AN ALLERGIC REACTION TO CEFAZOLIN FOR INJECTION OCCURS, DISCONTINUE TREATMENT WITH THE DRUG. SERIOUS ACUTE HYPERSENSITIVITY REACTIONS MAY REQUIRE TREATMENT WITH EPINEPHRINE AND OTHER EMERGENCY MEASURES, INCLUDING OXYGEN, IV FLUIDS, IV ANTIHISTAMINES, CORTICOSTEROIDS, PRESSOR AMINES, AND AIRWAY MANAGEMENT, AS CLINICALLY INDICATED.

Pseudomembranous colitis has been reported with nearly all antibacterial agents, including cefazolin, and may range in severity from mild to life-threatening. Therefore, it is important to consider this diagnosis in patients who present with diarrhea subsequent to the administration of antibacterial agents.

Treatment with antibacterial agents alters the normal flora of the colon and may permit overgrowth of clostridia. Studies indicate that a toxin produced by Clostridium difficile is a primary cause of “antibiotic-associated colitis.”

After the diagnosis of pseudomembranous colitis has been established, therapeutic measures should be initiated. Mild cases of pseudomembranous colitis usually respond to drug discontinuation alone. In moderate to severe cases, consideration should be given to management with fluids and electrolytes, protein supplementation, and treatment with an oral antibacterial drug clinically effective against C. difficile colitis.

PRECAUTIONS

General

Prolonged use of cefazolin may result in the overgrowth of nonsusceptible organisms. Careful clinical observation of the patient is essential.

When cefazolin is administered to patients with low urinary output because of impaired renal function, lower daily dosage is required (see DOSAGE AND ADMINISTRATION).

As with other beta-lactam antibiotics, seizures may occur if inappropriately high doses are administered to patients with impaired renal function (see DOSAGE AND ADMINISTRATION).

Cefazolin as with all cephalosporins, should be prescribed with caution in individuals with a history of gastrointestinal disease, particularly colitis.

Cephalosporins may be associated with a fall in prothrombin activity. Those at risk include patients with renal or hepatic impairment or poor nutritional state, as well as patients receiving a protracted course of antimicrobial therapy, and patients previously stabilized on anticoagulant therapy. Prothrombin time should be monitored in patients at risk and exogenous vitamin K administered as indicated.

Prescribing cefazolin in the absence of a proven or strongly suspected bacterial infection or a prophylactic indication is unlikely to provide benefit to the patient and increases the risk of the development of drug-resistant bacteria.

Drug Interactions

Probenecid may decrease renal tubular secretion of cephalosporins when used concurrently, resulting in increased and more prolonged cephalosporin blood levels.

Drug/Laboratory Test Interactions

A false positive reaction for glucose in the urine may occur with Benedict’s solution, Fehling’s solution or with CLINITEST® tablets, but not with enzyme-based tests such as CLINISTIX®.

Positive direct and indirect antiglobulin (Coombs) tests have occurred; these may also occur in neonates whose mothers received cephalosporins before delivery.

Information for Patients

Patients should be counseled that antibacterial drugs including cefazolin, should only be used to treat bacterial infections. They do not treat viral infections (e.g., the common cold). When cefazolin is prescribed to treat a bacterial infection, patients should be told that although it is common to feel better early in the course of therapy, the medication should be taken exactly as directed. Skipping doses or not completing the full course of therapy may: (1) decrease the effectiveness of the immediate treatment, and (2) increase the likelihood that bacteria will develop resistance and will not be treatable by cefazolin or other antibacterial drugs in the future.

Carcinogenesis/Mutagenesis

Mutagenicity studies and long-term studies in animals to determine the carcinogenic potential of cefazolin have not been performed.

Pregnancy

Teratogenic Effects

Reproduction studies have been performed in rats, mice, and rabbits at doses up to 25 times the human dose and have revealed no evidence of impaired fertility or harm to the fetus due to cefazolin. There are, however, no adequate and well-controlled studies in pregnant women. Because animal reproduction studies are not always predictive of human response, this drug should be used during pregnancy only if clearly needed.

Labor and Delivery

When cefazolin has been administered prior to caesarean section, drug levels in cord blood have been approximately one quarter to one third of maternal drug levels. The drug appears to have no adverse effect on the fetus.

Nursing Mothers

Cefazolin is present in very low concentrations in the milk of nursing mothers. Caution should be exercised when cefazolin is administered to a nursing woman.

Pediatric Use

Safety and effectiveness for use in premature infants and neonates have not been established. See DOSAGE AND ADMINISTRATION for recommended dosage in pediatric patients older than 1 month.

Geriatric Use

Of the 920 subjects who received cefazolin in clinical studies, 313 (34%) were 65 years and over, while 138 (15%) were 75 years and over. No overall differences in safety or effectiveness were observed between these subjects and younger subjects. Other reported clinical experience has not identified differences in responses between the elderly and younger patients, but greater sensitivity of some older individuals cannot be ruled out.

This drug is known to be substantially excreted by the kidney, and the risk of toxic reactions to this drug may be greater in patients with impaired renal function. Because elderly patients are more likely to have decreased renal function, care should be taken in dose selection, and it may be useful to monitor renal function (see PRECAUTIONS, General and DOSAGE AND ADMINISTRATION).

ADVERSE REACTIONS

The following reactions have been reported:

Gastrointestinal: Diarrhea, oral candidiasis (oral thrush), vomiting, nausea, stomach cramps, anorexia, and pseudomembranous colitis. Onset of pseudomembranous colitis symptoms may occur during or after antibiotic treatment (see WARNINGS). Nausea and vomiting have been reported rarely.

Allergic: Anaphylaxis, eosinophilia, itching, drug fever, skin rash, Stevens-Johnson syndrome.

Hematologic: Neutropenia, leukopenia, thrombocytopenia, thrombocythemia.

Hepatic: Transient rise in SGOT, SGPT, and alkaline phosphatase levels has been observed. As with other cephalosporins, reports of hepatitis have been received.

Renal: As with other cephalosporins, reports of increased BUN and creatinine levels, as well as renal failure, have been received.

Local Reactions: Rare instances of phlebitis have been reported at site of injection.

Other Reactions: Genital and anal pruritus (including vulvar pruritus, genital moniliasis, and vaginitis).

To report SUSPECTED ADVERSE REACTIONS, contact Hospira, Inc. at 1-800-441-4100 or FDA at 1-800-FDA-1088 or www.fda.gov/medwatch.

DOSAGE AND ADMINISTRATION

Note: Cefazolin for Injection in the ADD-Vantage® Vial is intended for intravenous infusion.

Usual Adult Dosage

Type of Infection | Dose | Frequency
Moderate to severe infections | 500 mg to 1 gram | every 6 to 8 hours
Mild infections caused by susceptible; gram-positive cocci | 250 mg to 500 mg | every 8 hours
Acute, uncomplicated urinary; tract infections | 1 gram | every 12 hours
Pneumococcal pneumonia | 500 mg | every 12 hours
Severe, life-threatening infections; (e.g., endocarditis, septicemia) [In rare instances, doses of up to 12 grams of cefazolin for injection per day have been used.] | 1 gram to 1.5 grams | every 6 hours

Perioperative Prophylactic Use

To prevent postoperative infection in contaminated or potentially contaminated surgery, recommended doses are:

a. 1 gram intravenous administered 1/2 hour to 1 hour prior to the start of surgery.
b. For lengthy operative procedures (e.g., 2 hours or more), 500 mg to 1 gram intravenous during surgery (administration modified depending on the duration of the operative procedure).
c. 500 mg to 1 gram intravenous every 6 to 8 hours for 24 hours postoperatively.

It is important that (1) the preoperative dose be given just (1/2 to 1 hour) prior to the start of surgery so that adequate antibiotic levels are present in the serum and tissues at the time of initial surgical incision; and (2) cefazolin for injection be administered, if necessary, at appropriate intervals during surgery to provide sufficient levels of the antibiotic at the anticipated moments of greatest exposure to infective organisms.

In surgery where the occurrence of infection may be particularly devastating (e.g., open-heart surgery and prosthetic arthroplasty), the prophylactic administration of cefazolin for injection may be continued for 3 to 5 days following the completion of surgery.

Dosage Adjustment for Patients with Reduced Renal Function

Cefazolin for injection may be used in patients with reduced renal function with the following dosage adjustments: Patients with a creatinine clearance of 55 mL/min. or greater or a serum creatinine of 1.5 mg% or less can be given full doses. Patients with creatinine clearance rates of 35 to 54 mL/min. or serum creatinine of 1.6 to 3 mg% can also be given full doses but dosage should be restricted to at least 8 hour intervals. Patients with creatinine clearance rates of 11 to 34 mL/min. or serum creatinine of 3.1 to 4.5 mg% should be given 1/2 the usual dose every 12 hours. Patients with creatinine clearance rates of 10 mL/min. or less or serum creatinine of 4.6 mg% or greater should be given 1/2 the usual dose every 18 to 24 hours. All reduced dosage recommendations apply after an initial loading dose appropriate to the severity of the infection. Patients undergoing peritoneal dialysis: See CLINICAL PHARMACOLOGY.

Pediatric Dosage

In pediatric patients, a total daily dosage of 25 to 50 mg per kg (approximately 10 to 20 mg per pound) of body weight, divided into 3 or 4 equal doses, is effective for most mild to moderately severe infections. Total daily dosage may be increased to 100 mg per kg (45 mg per pound) of body weight for severe infections. Since safety for use in premature infants and in neonates has not been established, the use of cefazolin for injection in these patients is not recommended.

Pediatric Dosage Guide
Weight |  | 25 mg/kg/day; Divided into 3 Doses |  | 25 mg/kg/day; Divided into 4 Doses
Lbs | Kg | Approximate Single Dose mg/every 8 hours | Vol. (mL) needed with dilution of 125 mg/mL | Approximate Single Dose mg/every 6 hours | Vol. (mL) needed with dilution of 125 mg/mL
10 | 4.5 | 40 mg | 0.35 mL | 30 mg | 0.25 mL
20 | 9 | 75 mg | 0.60 mL | 55 mg | 0.45 mL
30 | 13.6 | 115 mg | 0.90 mL | 85 mg | 0.70 mL
40 | 18.1 | 150 mg | 1.20 mL | 115 mg | 0.90 mL
50 | 22.7 | 190 mg | 1.50 mL | 140 mg | 1.10 mL

Weight |  | 50 mg/kg/day; Divided into 3 Doses |  | 50 mg/kg/day; Divided into 4 Doses
Lbs | Kg | Approximate Single Dose mg/every 8 hours | Vol. (mL) needed with dilution of 225 mg/mL | Approximate Single Dose mg/every 6 hours | Vol. (mL) needed with dilution of 225 mg/mL
10 | 4.5 | 75 mg | 0.35 mL | 55 mg | 0.25 mL
20 | 9 | 150 mg | 0.70 mL | 110 mg | 0.50 mL
30 | 13.6 | 225 mg | 1 mL | 170 mg | 0.75 mL
40 | 18.1 | 300 mg | 1.35 mL | 225 mg | 1 mL
50 | 22.7 | 375 mg | 1.70 mL | 285 mg | 1.25 mL

In pediatric patients with mild to moderate renal impairment (creatinine clearance of 70 to 40 mL/min.), 60 percent of the normal daily dose given in equally divided doses every 12 hours should be sufficient. In patients with moderate impairment (creatinine clearance of 40 to 20 mL/min.), 25 percent of the normal daily dose given in equally divided doses every 12 hours should be adequate. Pediatric patients with severe renal impairment (creatinine clearance of 20 to 5 mL/min.) may be given 10 percent of the normal daily dose every 24 hours. All dosage recommendations apply after an initial loading dose.

RECONSTITUTION

Preparation of Parenteral Solution

Parenteral drug products should be SHAKEN WELL when reconstituted, and inspected visually for particulate matter prior to administration. If particulate matter is evident in reconstituted fluids, the drug solutions should be discarded.

When reconstituted or diluted according to the instructions below, cefazolin is stable for 24 hours at room temperature. Reconstituted solutions may range in color from pale yellow to yellow without a change in potency.

ADD-Vantage® Vials of cefazolin for injection are to be reconstituted only with 0.9% Sodium Chloride Injection or 5% Dextrose Injection in the 50 mL or 100 mL ADD-Vantage® Flexible Diluent Containers or with 0.45% Sodium Chloride Injection in the 50 mL ADD-Vantage® Flexible Diluent Container. Cefazolin for injection supplied in single dose ADD-Vantage® Vials should prepared as directed below.

INSTRUCTIONS FOR USE

To Open Diluent Container:

Peel overwrap at corner and remove solution container. Some opacity of the plastic due to moisture absorption during the sterilization process may be observed. This is normal and does not affect the solution quality or safety. The opacity will diminish gradually.

To Assemble Vial and Flexible Diluent Container:

(Use Aseptic Technique)

1. Remove the protective covers from the top of the vial and the vial port on the diluent container as follows:
  a. To remove the breakaway vial cap, swing the pull ring over the top of the vial and pull down far enough to start the opening (see Figure 1), then pull straight up to remove the cap (see Figure 2).
  NOTE: Once the breakaway cap has been removed, do not access vial with syringe.
  b. To remove the vial port cover, grasp the tab on the pull ring, pull up to break the three tie strings, then pull back to remove the cover (see Figure 3).
2. Screw the vial into the vial port until it will go no further. THE VIAL MUST BE SCREWED IN TIGHTLY TO ASSURE A SEAL. This occurs approximately 1/2 turn (180°) after the first audible click (see Figure 4). The clicking sound does not assure a seal; the vial must be turned as far as it will go.
  NOTE: Once vial is seated, do not attempt to remove (see Figure 4).
3. Recheck the vial to assure that it is tight by trying to turn it further in the direction of assembly.
4. Label appropriately.

To Reconstitute the Drug:

1. Squeeze the bottom of the diluent container gently to inflate the portion of the container surrounding the end of the drug vial.
2. With the other hand, push the drug vial down into the container telescoping the walls of the container. Grasp the inner cap of the vial through the walls of the container (see Figure 5).
3. Pull the inner cap from the drug vial (see Figure 6). Verify that the rubber stopper has been pulled out, allowing the drug and diluent to mix.
4. Mix container contents thoroughly and use within the specified time.

Preparation for Administration:

(Use Aseptic Technique)

1. Confirm the activation and admixture of vial contents.
2. Check for leaks by squeezing container firmly. If leaks are found, discard unit as sterility may be impaired.
3. Close flow control clamp of administration set.
4. Remove cover from outlet port at bottom of container.
5. Insert piercing pin of administration set into port with a twisting motion until the pin is firmly seated.
  NOTE: See full directions on administration set carton.
6. Lift the free end of the hanger loop on the bottom of the vial, breaking the two tie strings. Bend the loop outward to lock it in the upright position, then suspend container from hanger.
7. Squeeze and release drip chamber to establish proper fluid level in chamber.
8. Open flow control clamp and clear air from set. Close clamp.
9. Attach set to venipuncture device. If device is not indwelling, prime and make venipuncture.
10. Regulate rate of administration with flow control clamp.

WARNING: Do not use flexible container in series connections.

Compatibility and Stability

Ordinarily ADD-Vantage® Vials should be reconstituted only when it is certain that the patient is ready to receive the drug. However, Cefazolin for Injection in ADD-Vantage® vials is stable for 24 hours at room temperature when reconstituted as directed (see RECONSTITUTION, ADD-Vantage® Vials and INSTRUCTIONS FOR USE).

(DO NOT REFRIGERATE OR FREEZE CEFAZOLIN SODIUM IN ADD-VANTAGE® VIALS.)

Prior to administration parenteral drug products should be inspected visually for particulate matter and discoloration whenever solution and container permit.

HOW SUPPLIED

Each Cefazolin for Injection, USP ADD-Vantage® vial contains, cefazolin sodium equivalent to 1 gram of cefazolin.

It is supplied in packages of 25 (NDC 0409-2585-01).

As with other cephalosporins, Cefazolin for Injection, USP tends to darken depending on storage conditions; within the stated recommendations, however, product potency is not adversely affected.

Before reconstitution, protect from light and store at 20° to 25°C (68° to 77°F) [see USP Controlled Room Temperature].

CLINITEST® is a registered trademark of Miles, Inc.

CLINISTIX® is a registered trademark of Bayer Corporation.

Revised: September 2020

46276359

Manufactured by Sandoz GmbH for

Hospira, Inc., Lake Forest, IL 60045, USA

PACKAGE/LABEL PRINCIPAL DISPLAY PANEL

NDC 0409-2585-01

Cefazolin for Injection, USP

1 gram per ADD-Vantage® Vial

Equivalent to 1 gram cefazolin

For Intravenous Infusion Only

Note: For use only with ADD-Vantage® Flexible Diluent Container.

PROTECT FROM LIGHT.

RETAIN IN CARTON UNTIL TIME OF USE.

25 x 1 gram Single-Dose ADD-Vantage® Vials

Hospira